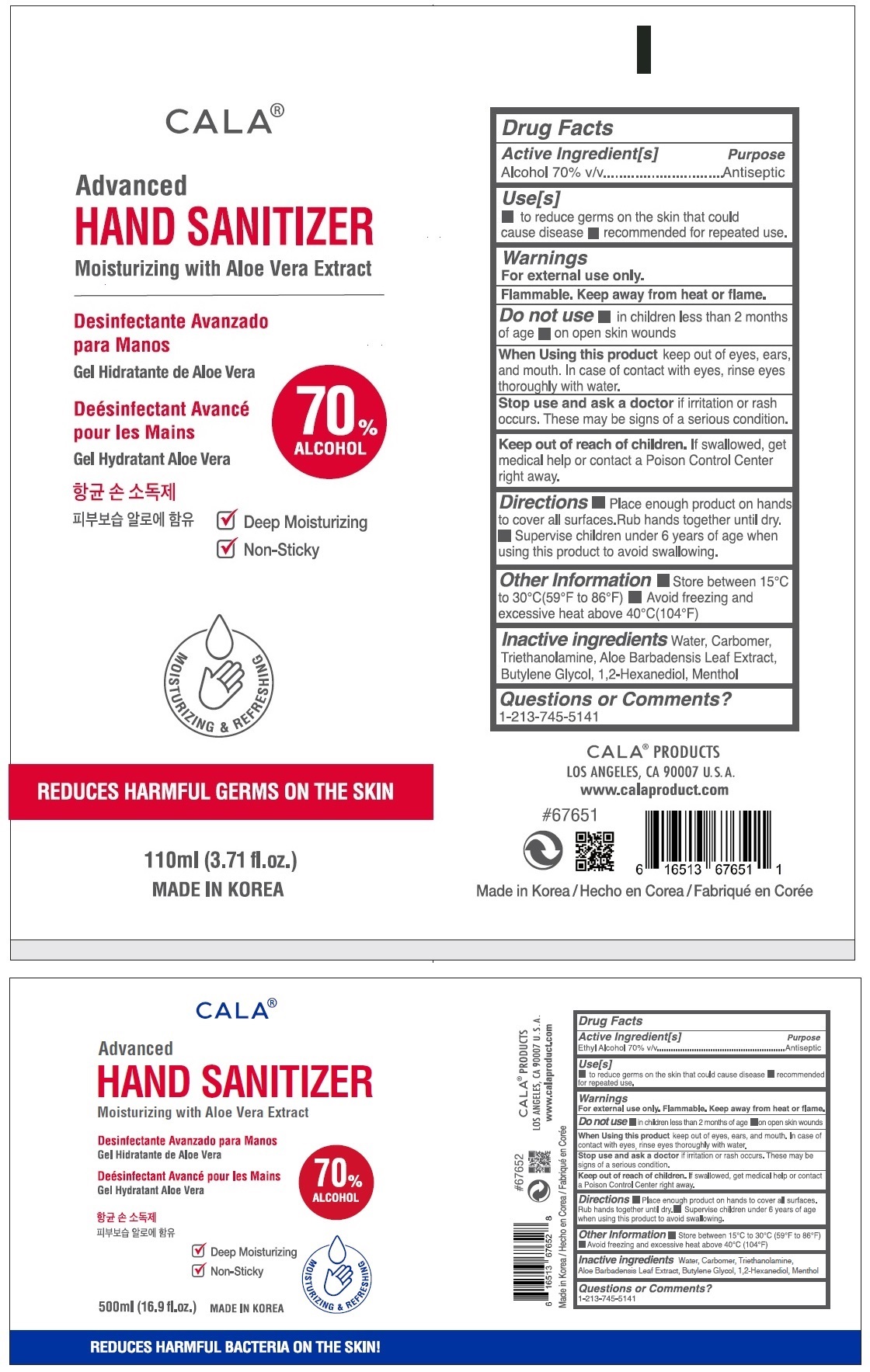 DRUG LABEL: CALA ADVANCED HAND SANITIZER
NDC: 58241-0009 | Form: GEL
Manufacturer: David Cosmetic Co Ltd
Category: otc | Type: HUMAN OTC DRUG LABEL
Date: 20211013

ACTIVE INGREDIENTS: ALCOHOL 70 mL/100 mL
INACTIVE INGREDIENTS: WATER; CARBOMER HOMOPOLYMER, UNSPECIFIED TYPE; TROLAMINE; ALOE VERA LEAF; BUTYLENE GLYCOL; 1,2-HEXANEDIOL; MENTHOL, UNSPECIFIED FORM

Active Ingredient [s]

Alcohol 70% v/v

Purpose

Antiseptic

Use[s]

▪ to reduce bacteria on the skin that could cause disease ▪ recommended for repeated use.

Warnings

For external use only.

Flammable. Keep away from heat or flame.

Do not use ▪ in children less than 2 months of age ▪ on open skin wounds

When using this product keep out of eyes, ears and mouth. In case of contact with eyes, rinse eyes thoroughly with water.

Stop use and ask a doctor if irritation or rash occurs. These may be signs of a serious condition.

Keep out of reach of children. If swallowed, get medical help or contact a Poison Control Center right away.

DOSAGE AND ADMINISTRATION

Directions ▪ Place enough product on hands to cover all surfaces.Rub hands together until dry. ▪ Supervise children under 6 years of age when using this product to avoid swallowing.

Other Information ▪ Store between 15°C to 30°C(59°F to 86°F) ▪ Avoid freezing and excessive heat above 40°C(104°F)

INACTIVE INGREDIENT

Inactive ingredients Water, Carbomer, Triethanolamine, Aloe Barbadensis Leaf Extract, Butylene Glycol, 1,2-Hexanediol, Menthol

Questions or Comments?

1-213-745-5141

Gel Hydratant Aloe Vera

√ Deep Moisturizing

√ Non-Sticky

MOISTURISING & REFRESHING

KILLS HARMFUL GERM ON THE SKIN!

MADE IN KOREA

CALA® PRODUCTS

LOS ANGELES, CA 90007, U.S.A.

www.calaproduct.com